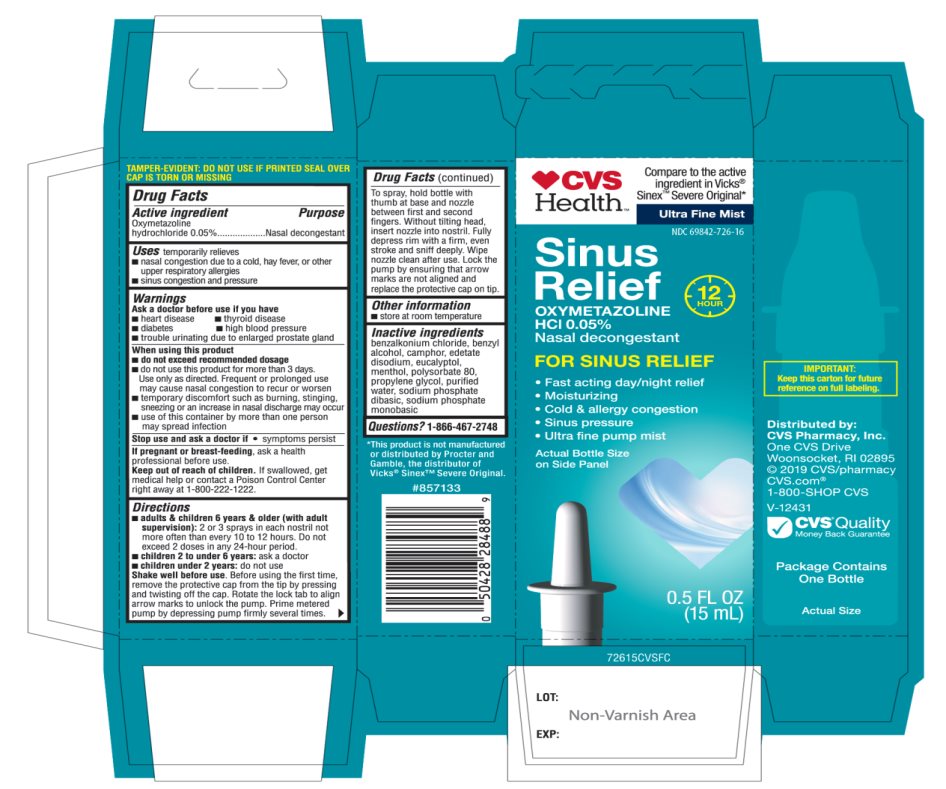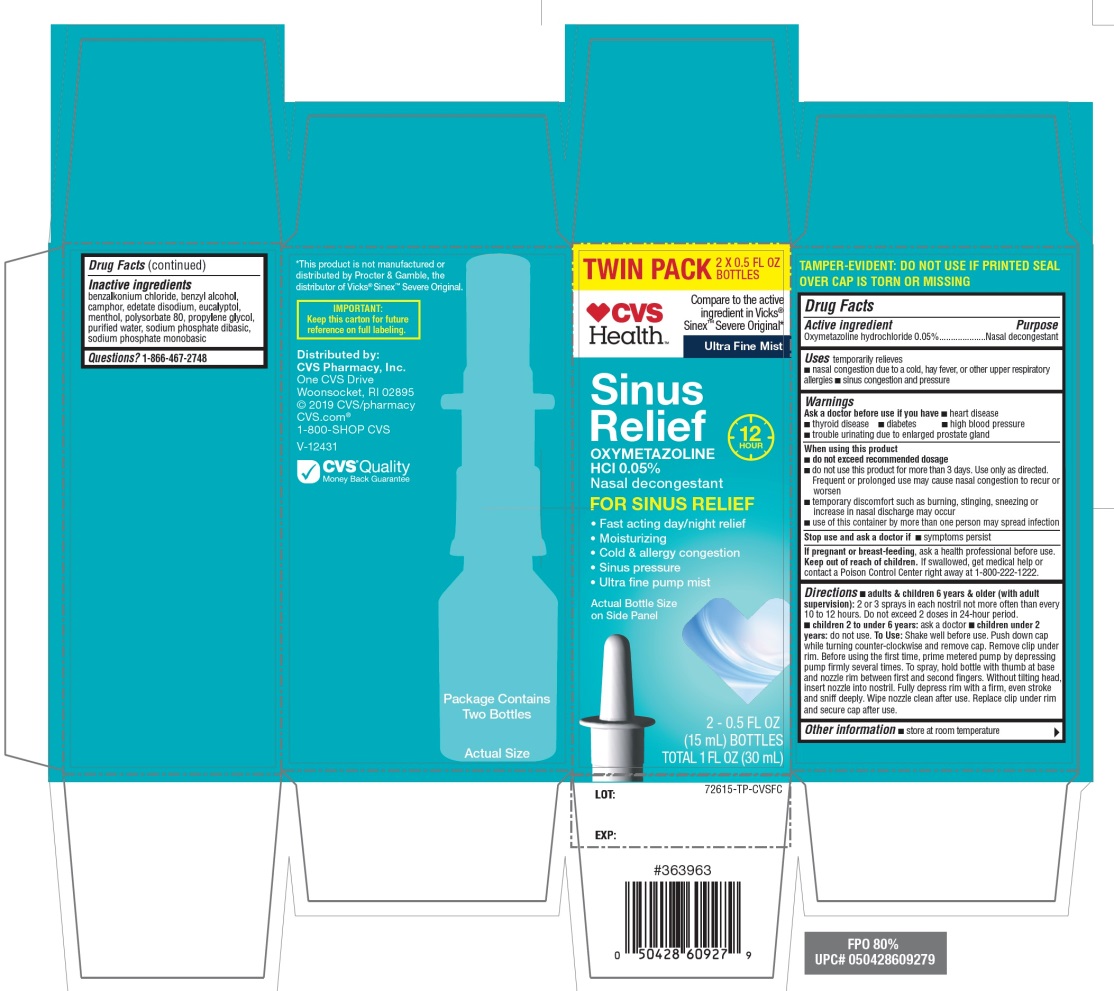 DRUG LABEL: CVS Health

NDC: 69842-726 | Form: SPRAY
Manufacturer: CVS PHARMACY, INC.
Category: otc | Type: HUMAN OTC DRUG LABEL
Date: 20251209

ACTIVE INGREDIENTS: OXYMETAZOLINE HYDROCHLORIDE 0.05 g/100 mL
INACTIVE INGREDIENTS: BENZALKONIUM CHLORIDE; BENZYL ALCOHOL; CAMPHOR (NATURAL); EDETATE DISODIUM; EUCALYPTOL; MENTHOL, UNSPECIFIED FORM; POLYSORBATE 80; PROPYLENE GLYCOL; WATER; SODIUM PHOSPHATE, DIBASIC, UNSPECIFIED FORM; SODIUM PHOSPHATE, MONOBASIC, UNSPECIFIED FORM

CVS Health™Sinus Relief Drug Facts

Active ingredient

Oxymetazoline hydrochloride 0.05%

Purpose

Nasal Decongestant

Uses

temporarily relieves

- nasal congestion due to a cold, heavy fever, or other upper respiratory allergies
- Sinus congestion and pressure

Ask a doctor before use if you have

- heart disease
- high blood pressure
- diabetes
- thyroid disease
- trouble urinating due to an enlarged prostate gland

When using this product

- do not exceed recommended dosage
- do not use this product for more than 3 days. Use only as directed. Frequent or prolonged use may cause nasal congestion to recur or worsen.
- temporary discomfort such as burning, stinging, sneezing or an increase in nasal discharge may occur
- use of this container by more than one person may spread infection

Stop use and ask a doctor if

- symptoms persist

If pregnant or breast-feeding,

ask a health professional before use.

Keep out of reach of children.

If swallowed, get medical help or contact a Poison Control Center right away at (1-800-222-1222).

Directions

- adults & children 6 years & older (with adult supervision):2 or 3 sprays in each nostril not more often than every 10 to 12 hours. Do not exceed 2 doses in any 24-hour period.
- Children 2 to under 6 years:ask a doctor
- Children 2 years:do not use

To Use:Shake well before use .Push down cap while turning counter-clockwise and remove cap. Remove clip under rim. Before using the first time, prime metered pump by depressing pump firmly several times. To spray, hold bottle with thumb at base and nozzle between first and second fingers without titling head, insert nozzle into nostril. Fully depress rim with a firm, even stroke and sniff deeply. Wipe nozzle clean after use. Replace clip under rim and secure cap after use.

Other information

- store at room temperature

Inactive ingredients

benzalkonium chloride, benzyl alcohol, camphor, edetate disodium, eucalyptol, menthol, polysorbate 80, propylene glycol, purified water, sodium phosphate dibasic, sodium phosphate monobasic.

Questions or comments?

1-866-467-2748

Principal Display Panel

CVS Health™

Compare to the active ingredient in Vicks® Sinex™ Severe Original*

Ultra-Fine Mist

12 HOUR

Sinus Relief

OXYMETAZOLINE HCl 0.05%

Nasal decongestant

FOR SINUS RELIEF

- Fast acting day/night relief
- Moisturizing
- Cold & allergy congestion
- Sinus pressure
- Ultra fine pump mist

Actual Bottle Size on Side Panel

IMPORTANT: KEEP THE CARTON FOR FUTURE REFERENCE ON FULL LABELING

Distributed by:

CVS Pharmacy, Inc.

One CVS Drive, Woonsocket, RI 02895

2019 CVS/pharmacy

CVS.com

1-800-SHOP CVS, V-12431

- CVS Quality
  Money Back Guarantee
  Package contains One Bottle B

*This product is not manufactured or distributed by Procter and Gamble, the distributer of Vicks®Sinex™ Severe Original.

PACKAGE LABEL 15 mL